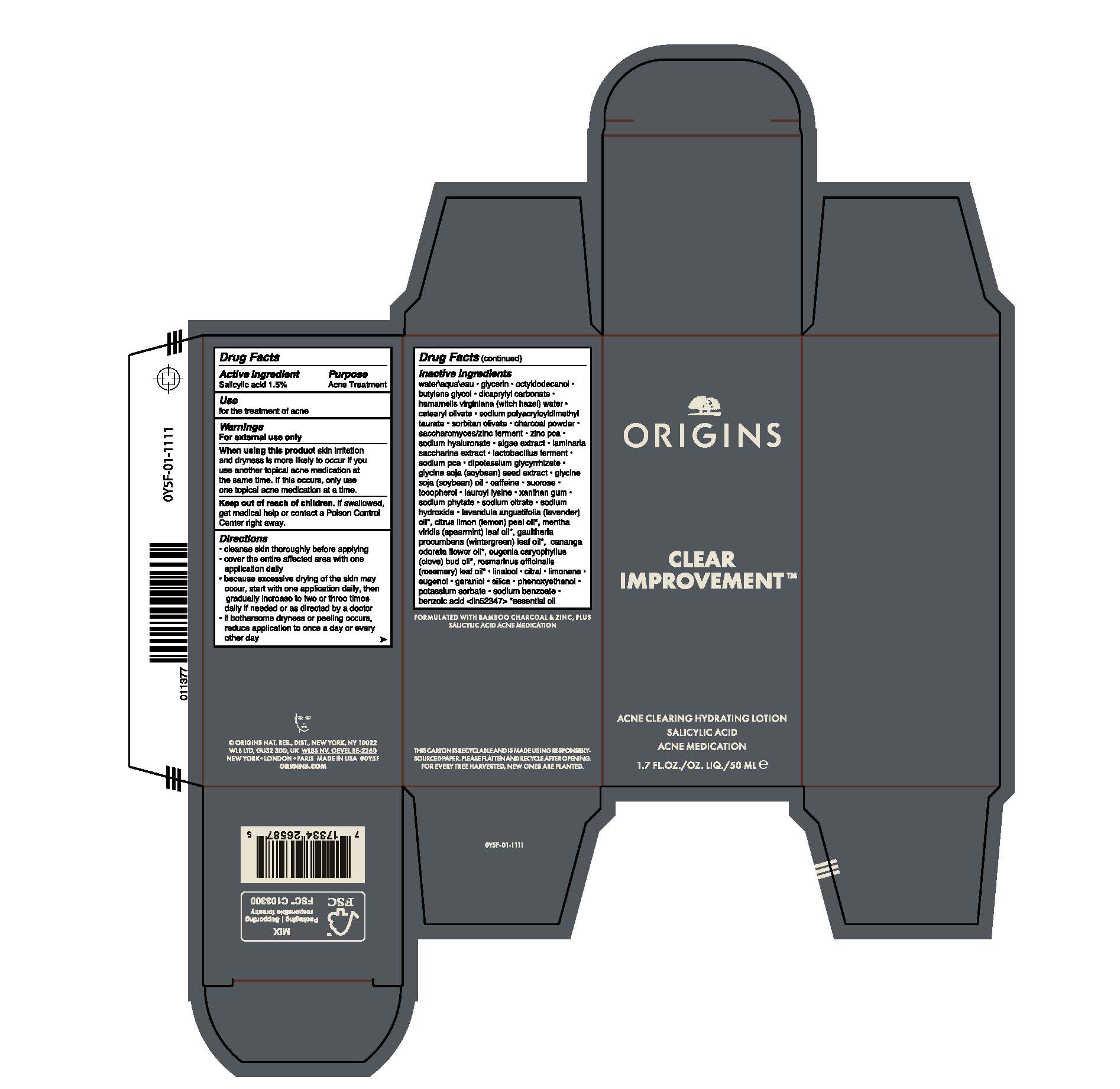 DRUG LABEL: CLEAR IMPROVEMENT ACNE CLEARING HYDRATING LTN
NDC: 59427-117 | Form: LOTION
Manufacturer: ORIGINS NATURAL RESOURCES INC.
Category: otc | Type: HUMAN OTC DRUG LABEL
Date: 20240205

ACTIVE INGREDIENTS: SALICYLIC ACID 15 mg/1 mL
INACTIVE INGREDIENTS: SACCHARINA LATISSIMA; GLYCYRRHIZINATE DIPOTASSIUM; CETEARYL OLIVATE; BUTYLENE GLYCOL; DICAPRYLYL CARBONATE; LAUROYL LYSINE; CAFFEINE; TOCOPHEROL; METHYL SALICYLATE; ROSEMARY OIL; LEMON OIL; SPEARMINT OIL; CANANGA OIL; OCTYLDODECANOL; HAMAMELIS VIRGINIANA TOP WATER; POTASSIUM SORBATE; SUCROSE; XANTHAN GUM; PHENOXYETHANOL; WATER; SOYBEAN OIL; LIMONENE, (+)-; GERANIOL; PORPHYRIDIUM PURPUREUM; SODIUM PYRROLIDONE CARBOXYLATE; CLOVE OIL; CITRAL; SILICON DIOXIDE; GLYCERIN; SODIUM POLYACRYLOYLDIMETHYL TAURATE; SORBITAN OLIVATE; ACTIVATED CHARCOAL; ZINC PIDOLATE; HYALURONATE SODIUM; SOYBEAN; SODIUM CITRATE; SODIUM HYDROXIDE; LAVENDER OIL; LINALOOL, (+/-)-; EUGENOL; SODIUM BENZOATE; BENZOIC ACID

CLEAR IMPROVEMENT ACNE CLEARING HYDRATING LOTION

Active Ingredient

Salicylic Acid 1.5%

Purpose

Acne Treatment

Use

for the treatmenet of acne

Warnings

For External use only

When using this product

skin irritattion and dryness is more likely to occur if you use another topical acne medication at the same time. If this occurs, only use one topical acne medication at a time.

Keep out of reach of children

If swallowed, get medical help or contact a poison control center right away.

Directions

Cleanse skin throughly before applying

Cover the entire affected area with one application daily

Because excessive drying of the skin may occur, start with one application daily, then gradually increase to two or three times daily if needed or as directed by a doctor.

If bothersome dryness or peeling occurs, reduce application to once a day or every other day

Inactive Ingredients

water\aqua\eau,glycerin,octyldodecanol,butylene glycol,dicaprylyl carbonate,hamamelis virginiana (witch hazel) water,cetearyl olivate,sodium polyacryloyldimethyl taurate,sorbitan olivate,charcoal powder,saccharomyces/zinc ferment,zinc pca,sodium hyaluronate,algae extract,laminaria saccharina extract,lactobacillus ferment,sodium pca,dipotassium glycyrrhizate,glycine soja (soybean) seed extract,glycine soja (soybean) oil,caffeine,sucrose,tocopherol,lauroyl lysine,xanthan gum,sodium phytate,sodium citrate,sodium hydroxide,lavandula angustifolia (lavender) oil*, citrus limon (lemon) peel oil*, mentha viridis (spearmint) leaf oil*, gaultheria procumbens (wintergreen) leaf oil*, cananga odorata flower oil*, eugenia caryophyllus (clove) bud oil*, rosmarinus officinalis (rosemary) leaf oil*,linalool,citral,limonene,eugenol,geraniol,silica,phenoxyethanol,potassium sorbate,sodium benzoate,benzoic acid <iln52347>
* essential oil

PACKAGE LABEL

ORIGINS

CLEAR IMPROVEMENT

ACNE CLEANSING HYDRATING LOTION

SALICYLIC ACID

ACNE MEDICATION

1.7 FL.OZ./OZ.LIQ/50ML